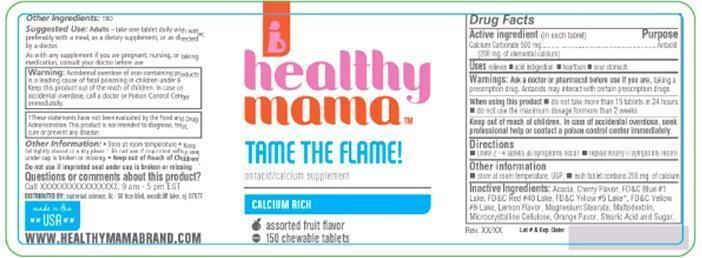 DRUG LABEL: healthy mama
NDC: 58154-103 | Form: TABLET, CHEWABLE
Manufacturer: MATERNAL SCIENCE, LLC
Category: otc | Type: HUMAN OTC DRUG LABEL
Date: 20130531

ACTIVE INGREDIENTS: CALCIUM CARBONATE 500 mg/1 1
INACTIVE INGREDIENTS: SUCROSE; STEARIC ACID; MAGNESIUM STEARATE; ACACIA; MALTODEXTRIN; CELLULOSE, MICROCRYSTALLINE; FD&C YELLOW NO. 5; FD&C RED NO. 40; FD&C BLUE NO. 1; FD&C YELLOW NO. 6

Drug Facts

Active ingredient (in each tablet)

Calcium Carbonate 500 mg

(200 mg. of elemental calcium)

Purposes

Antacid

Uses

relieves

- acid indigestion
- heartburn
- sour stomach

Warnings

Ask a doctor or pharmacist before use if you are, taking a prescription drug. Antacids may interact with certain prescription drugs.

WHEN USING

- do not take more than 16 tablets in 24 hours
- do not use the maximum dosage for more than 2 weeks

Keep out of reach of children. In case of accidental overdose, seek professional help or contact a poison control center immediately.

Directions

- chew 2-4 tablets as symptoms occur
- repeat hourly if symptoms return

Other information

- Store at room temperature, USP.
- each tablet contains 200 mg. of calcium

Inactive ingredients

Acacia, Colloidal Silica, Magnesium Stearate, Maltodextrin, Microcrystalline Cellulose, Natural and Artificial Spearmint Flavor, Starch, Sucrose

Questions or comments?

Call xxxxxxxxxx, 9 am- 5 pm EST

Principal Display Panel

healthy

mama

TAME THE FLAME!

antacid calcium supplement

CALCIUM RICH

assorted fruit flavor

150 chewable tablets